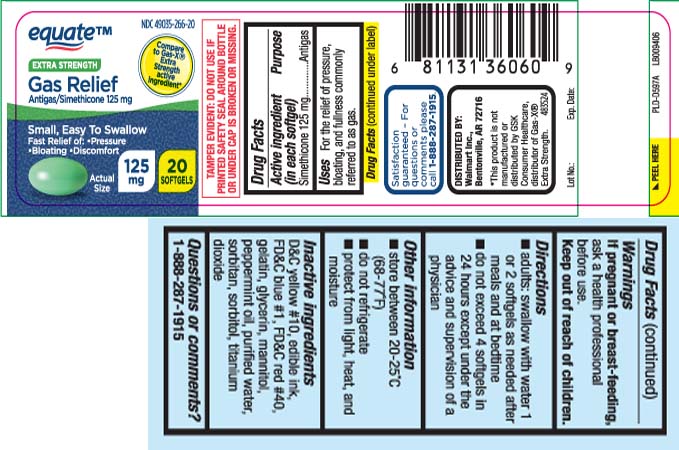 DRUG LABEL: Gas Relief
NDC: 49035-266 | Form: CAPSULE, LIQUID FILLED
Manufacturer: EQUATE (Wal-Mart Stores, Inc.) (see also WAL-MART INC)
Category: otc | Type: HUMAN OTC DRUG LABEL
Date: 20251119

ACTIVE INGREDIENTS: DIMETHICONE 125 mg/1 1
INACTIVE INGREDIENTS: D&C YELLOW NO. 10; FD&C BLUE NO. 1; FD&C RED NO. 40; GELATIN; GLYCERIN; PEPPERMINT OIL; WATER; SORBITAN; SORBITOL; TITANIUM DIOXIDE; MANNITOL

Drug Facts

Active ingredient (in each softgel)

Simethicone 125 mg

Purpose

Antigas

Uses

- for the relief of pressure, bloating, and fullness commonly referred to as gas

Warnings

If pregnant or breast-feeding,

ask a health professional before use.

Directions

- adults: swallow with water 1 or 2 softgels as needed after meals and at bedtime
- do not exceed 4 softgels in 24 hours except under the advise and supervision of a physician

Other information

- store between 20-25°C (68-77°F)
- do not refrigerate
- protect from light, heat, and moisture

Inactive ingredients

D&C yellow #10, edible ink, FD&C blue #1, FD&C red #40, gelatin, glycerin, mannitol, peppermint oil, purified water*, sorbitan*, sorbitol*, titanium dioxide

Questions or comments?

Call 1-888-287-1915

Principal Display Panel

Compare to Gas-X® Extra Strengthactive ingredient*

EXTRA STRENGTH

Gas Relief

Antigas/Simethicone 125 mg

Small, Easy To Swallow

Fast relief of

- Pressure
- Bloating
- Discomfort

SOFTGELS

TAMPER EVIDENT: DO NOT USE IF PRINTED SAFETY SEAL AROUND BOTTLE OR UNDER CAP IS BROKEN OR MISSING

†This product is not manufactured or distributed by GSK Consumer Healthcare, distributor of Gas- X® Extra Strength

Distributed by Walmart Inc,

Bentonville, AR 72716

Product Label

EQUATE Extra Strength Gas Relief